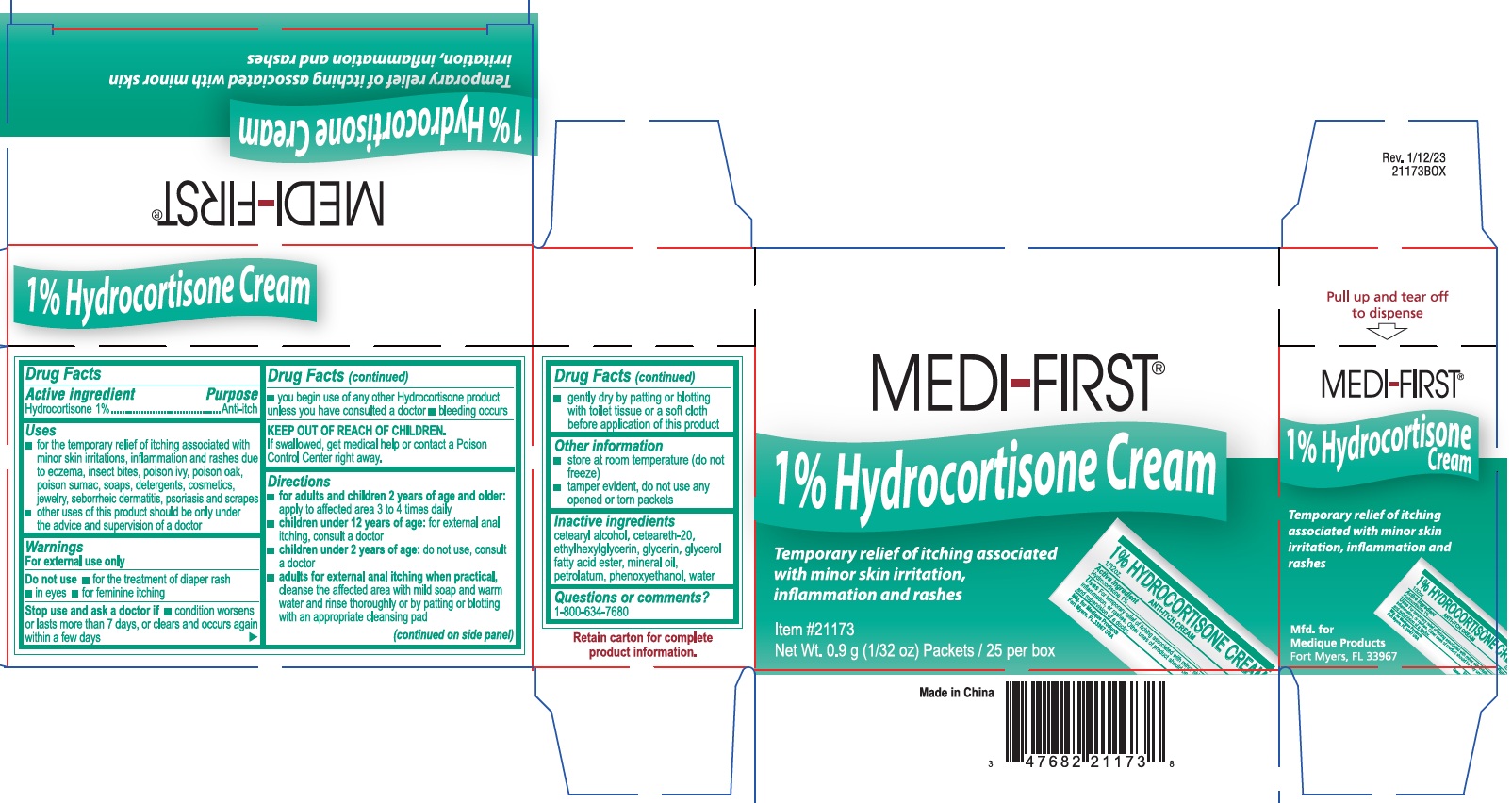 DRUG LABEL: MEDI-FIRST
NDC: 71927-032 | Form: CREAM
Manufacturer: Orazen Inc
Category: otc | Type: HUMAN OTC DRUG LABEL
Date: 20251212

ACTIVE INGREDIENTS: HYDROCORTISONE ACETATE 10 mg/1 g
INACTIVE INGREDIENTS: PETROLATUM; POLYOXYL 20 CETOSTEARYL ETHER; CETOSTEARYL ALCOHOL; ETHYLHEXYLGLYCERIN; PHENOXYETHANOL; GLYCERIN; MINERAL OIL; WATER

71927-032_ MEDI-FIRST
Hydrocortisone Cream 1%

Active ingredient

Hydrocortisone 1%

Purpose

Anti-itch

Uses

- for the temporary relief of itching associated with minor skin irritation,inflammation and rashed due to eczema, insect bites, poison ivy, poison oak,poison sumac, soaps, detergents, cosmetics,jewelry, sebortheic dermatitis, psoriasis and scrapes
- other uses of this product should be only under the advice and supervision of a doctor

Warnings

For external use only

Do not use

- for treatment of diaper rash
- in eyes
- for feminine itching

Stop use and ask a doctor if

- condition worsens or lasts more than 7 days, or clears up and occurs again within a few days
- you begin use of any other hydrocortisone product
- bleeding occurs

Keep out of reach of children.

If swallowed, get medical help or contact a Poison Control Center right away.

Directions

- for adults and children 2 years of age and older:apply to affected area 3 to 4 times daily
- children under 12 years of age:for external anal itching, consult a doctor
- children under 2 years of age:do not use, consult a doctor
- adults for external anal itching when practical,cleanse the affected area with mild soap and warm water and rinse thoroughly or by patting or blotting with an appropriate cleansing pad

(continued on side panel)

- gently dry by patting or blotting with toilet tissue or a soft cloth before application of this product

Other information

- store at room temperature (do not freeze)
- tamper evident, do not use any opened or torn packets

Inactive ingredients

cetearyl alcohol, ceteareth-20, ethylhexylglycerin, glycerin, glycerol fatty acid ester, mineral oil, petrolatum, phenoxyethanol, water

Questions or comments?

1-800-634-7680